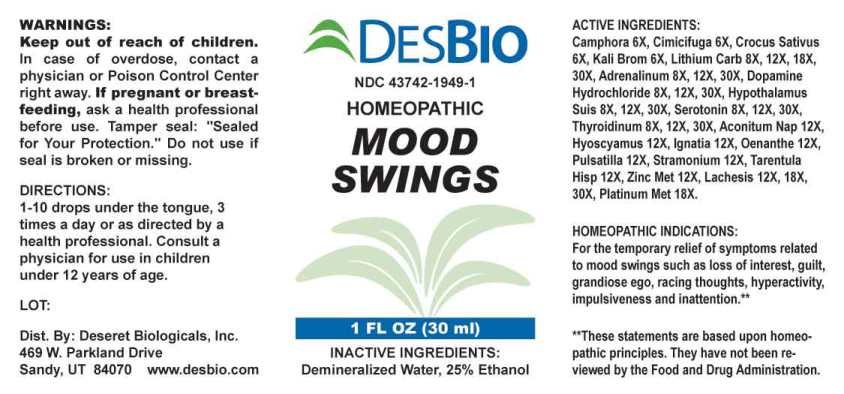 DRUG LABEL: Mood Swings
NDC: 43742-1949 | Form: LIQUID
Manufacturer: Deseret Biologicals, Inc.
Category: homeopathic | Type: HUMAN OTC DRUG LABEL
Date: 20240911

ACTIVE INGREDIENTS: CAMPHOR (NATURAL) 6 [hp_X]/1 mL; BLACK COHOSH 6 [hp_X]/1 mL; SAFFRON 6 [hp_X]/1 mL; POTASSIUM BROMIDE 6 [hp_X]/1 mL; LITHIUM CARBONATE 8 [hp_X]/1 mL; EPINEPHRINE 8 [hp_X]/1 mL; DOPAMINE HYDROCHLORIDE 8 [hp_X]/1 mL; SUS SCROFA HYPOTHALAMUS 8 [hp_X]/1 mL; SEROTONIN HYDROCHLORIDE 8 [hp_X]/1 mL; THYROID 8 [hp_X]/1 mL; ACONITUM NAPELLUS WHOLE 12 [hp_X]/1 mL; HYOSCYAMUS NIGER 12 [hp_X]/1 mL; STRYCHNOS IGNATII SEED 12 [hp_X]/1 mL; OENANTHE CROCATA ROOT 12 [hp_X]/1 mL; PULSATILLA PRATENSIS WHOLE 12 [hp_X]/1 mL; DATURA STRAMONIUM 12 [hp_X]/1 mL; LYCOSA TARANTULA 12 [hp_X]/1 mL; ZINC 12 [hp_X]/1 mL; LACHESIS MUTA VENOM 12 [hp_X]/1 mL; PLATINUM 18 [hp_X]/1 mL
INACTIVE INGREDIENTS: WATER; ALCOHOL

DRUG FACTS:

ACTIVE INGREDIENTS:

Camphora 6X, Cimicifuga Racemosa 6X, Crocus Sativus 6X, Kali Bromatum 6X, Lithium Carbonicum 8X, 12X, 18X, 30X, Adrenalinum 8X, 12X, 30X, Dopamine Hydrochloride 8X, 12X, 30X, Hypothalamus Suis 8X, 12X, 30X, Serotonin (Hydrochloride) 8X, 12X, 30X, Thyroidinum (Suis) 8X, 12X, 30X, Aconitum Napellus 12X, Hyoscyamus Niger 12X, Ignatia Amara 12X, Oenanthe Crocata 12X, Pulsatilla (Pratensis) 12X, Stramonium 12X, Tarentula Hispana 12X, Zincum Metallicum 12X, Lachesis Mutus 12X, 18X, 30X, Platinum Metallicum 18X.

HOMEOPATHIC INDICATIONS:

For temporary relief of symptoms related to Mood swings such as loss of interest, guilt, grandiose ego, racing thoughts, hyperactivity, impulsiveness and inattention.**

**These statements are based upon homeopathic principles. They have not been reviewed by the Food and Drug Administration.

WARNINGS:

Keep out of reach of children. In case of overdose, contact a physician or Poison Control Center right away.

If pregnant or breast-feeding, ask a health professional before use.

Tamper seal: "Sealed for Your Protection." Do not use if seal is broken or missing.

Keep out of reach of children. In case of overdose, contact a physician or Poison Control Center right away.

DIRECTIONS:

1-10 drops under the tongue, 3 times a day or as directed by a health professional. Consult a physician for use in children under 12 years of age.

HOMEOPATHIC INDICATIONS:

For temporary relief of symptoms related to Mood swings such as loss of interest, guilt, grandiose ego, racing thoughts, hyperactivity, impulsiveness and inattention.**

**These statements are based upon homeopathic principles. They have not been reviewed by the Food and Drug Administration.

INACTIVE INGREDIENTS:

Demineralized Water, 25% Ethanol

QUESTIONS:

Dist. By: Deseret Biologicals, Inc.
469 W. Parkland Drive
Sandy, UT 84070 www.desbio.com

PACKAGE LABEL DISPLAY:

DESBIO

NDC 43742-1949-1

HOMEOPATHIC

MOOD

SWINGS

1 FL OZ (30 ml)